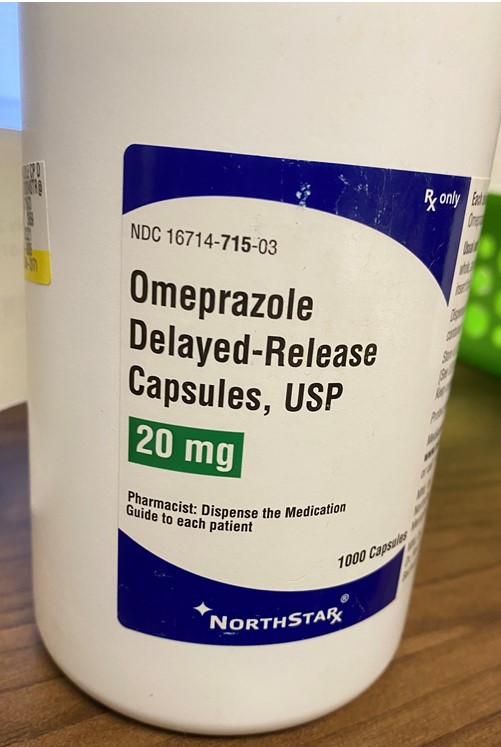 DRUG LABEL: Omeprazole
NDC: 80175-0715 | Form: CAPSULE, DELAYED RELEASE
Manufacturer: Central Packaging
Category: prescription | Type: HUMAN PRESCRIPTION DRUG LABEL
Date: 20210224

ACTIVE INGREDIENTS: OMEPRAZOLE 20 mg/1 1

INDICATIONS AND USAGE

1.1 Treatment of Active Duodenal Ulcer

Omeprazole delayed-release capsules are indicated for short-term treatment of active duodenal ulcer in adults. Most patients heal within four weeks. Some patients may require an additional four weeks of therapy.

1.2 Helicobacter pylori Eradication to Reduce the Risk of Duodenal Ulcer Recurrence

Eradication of H. pylori has been shown to reduce the risk of duodenal ulcer recurrence.

Triple Therapy

Omeprazole delayed-release capsules in combination with clarithromycin and amoxicillin, are indicated for treatment of patients with H. pylori infection and duodenal ulcer disease (active or up to 1-year history) to eradicate H. pylori in adults.

Dual Therapy

Omeprazole delayed-release capsules in combination with clarithromycin are indicated for treatment of patients with H. pylori infection and duodenal ulcer disease to eradicate H. pylori in adults.

Among patients who fail therapy, omeprazole delayed-release capsules are with clarithromycin is more likely to be associated with the development of clarithromycin resistance as compared with triple therapy. In patients who fail therapy, susceptibility testing should be done. If resistance to clarithromycin is demonstrated or susceptibility testing is not possible, alternative antimicrobial therapy should be instituted [see Clinical Pharmacology (12.4) and the clarithromycin prescribing information, Microbiology section].

1.3 Treatment of Active Benign Gastric Ulcer

Omeprazole delayed-release capsules are indicated for short-term treatment (4 to 8 weeks) of active benign gastric ulcer in adults.

1.4 Treatment of Symptomatic Gastroesophageal Reflux Disease (GERD)

Omeprazole delayed-release capsules are indicated for the treatment of heartburn and other symptoms associated with GERD for up to 4 weeks in patients 2 years of age and older.

1.5 Treatment of Erosive Esophagitis (EE) Due to Acid-Mediated GERD

Pediatric Patients 2 Years of Age to Adults

Omeprazole delayed-release capsules are indicated for the short-term treatment (4 to 8 weeks) of EE due to acid-mediated GERD that has been diagnosed by endoscopy in patients 2 years of age and older.

The efficacy of omeprazole delayed-release capsules used for longer than 8 weeks in patients with EE has not been established. If a patient does not respond to 8 weeks of treatment, an additional 4 weeks of treatment may be given. If there is recurrence of EE or GERD symptoms (e.g., heartburn), additional 4 to 8 week courses of omeprazole delayed-release capsules may be considered.

1.6 Maintenance of Healing of EE Due to Acid-Mediated GERD

Omeprazole delayed-release capsules are indicated for the maintenance healing of EE due to acid-mediated GERD in patients 2 years of age and older.

Controlled studies do not extend beyond 12 months.

1.7 Pathological Hypersecretory Conditions

Omeprazole delayed-release capsules are indicated for the long-term treatment of pathological hypersecretory conditions (e.g., Zollinger-Ellison syndrome, multiple endocrine adenomas and systemic mastocytosis) in adults.